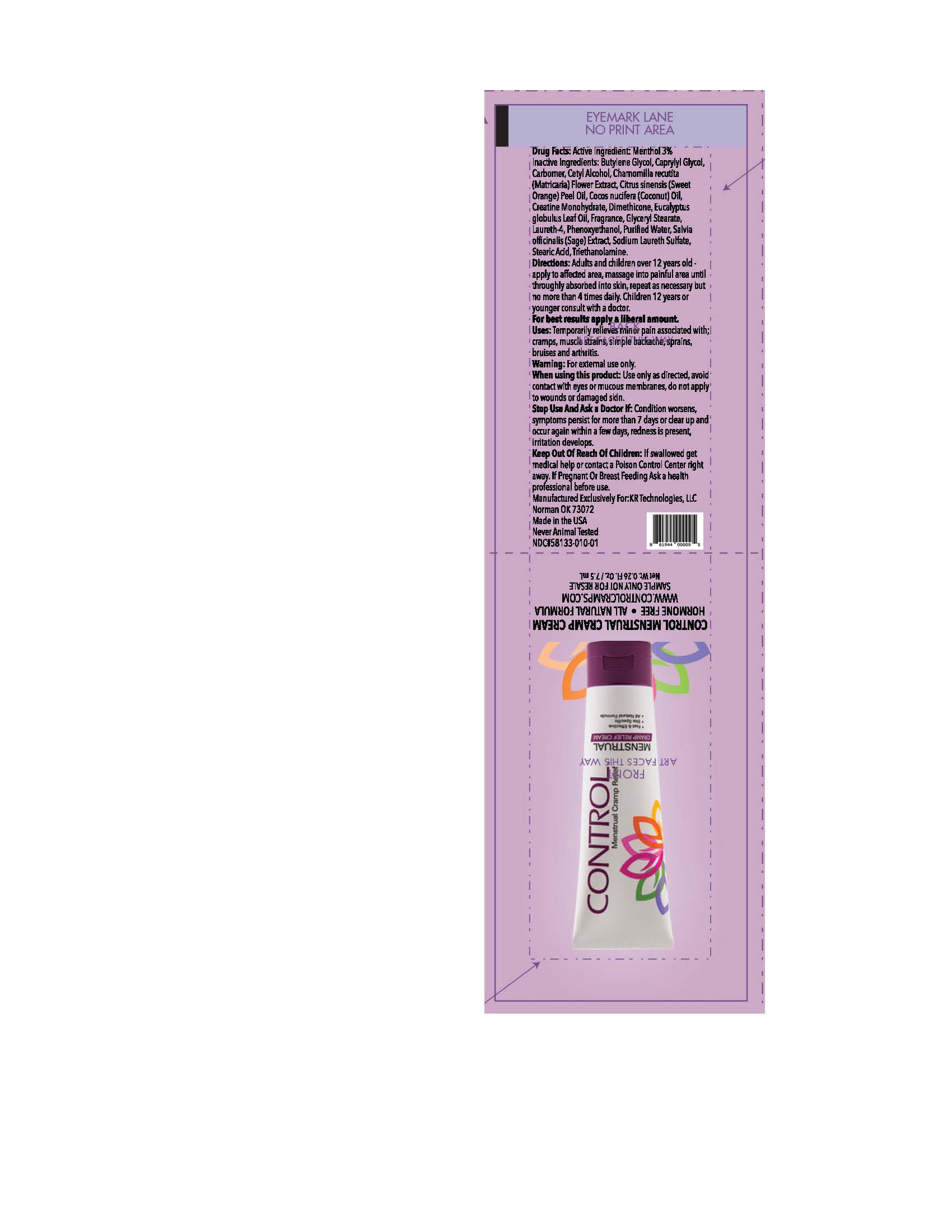 DRUG LABEL: Control Menstrual Cramp Relief
NDC: 58133-010 | Form: CREAM
Manufacturer: Cosmetic Specialty Labs, Inc.
Category: otc | Type: HUMAN OTC DRUG LABEL
Date: 20230524

ACTIVE INGREDIENTS: MENTHOL 3 g/100 mL
INACTIVE INGREDIENTS: PHENOXYETHANOL; WATER; CHAMOMILE; ORANGE OIL, COLD PRESSED; COCONUT OIL; BUTYLENE GLYCOL; CAPRYLYL GLYCOL; CETYL ALCOHOL; LAURETH-4; STEARIC ACID; GLYCERYL STEARATE SE; SAGE OIL; CREATINE MONOHYDRATE; TROLAMINE; DIMETHICONE; EUCALYPTUS OIL; SODIUM LAURETH SULFATE; CARBOMER 940

KRT packet

Active Ingredient

Menthol, 3.0%

Purpose

Topical analgesic

Uses

temporarily relieves minor pain associated with: • arthritis • simple backache • muscle strains • sprains • bruises • cramps

Warnings

for external use only

When using this product use only as directed • avoid contact with eyes or mucous membranes • do not apply to wounds or damaged skin

Stop use and ask a doctor if• condition worsens • symptoms persist for more than 7 days or clear up and occur again within a few days • redness is present • irritation develeps

PREGNANCY OR BREAST FEEDING

If pregnant or breast-feeding, ask a health professional before use.

Keep out of reach of children. If swallowed, get medical help or contact Poison Control Center right away.

Directions

Adults and children over 12 years:• apply to affected area • massage into painful area until throughly absorbed into skin • repeat as necessary, but no more than 4 time daily

Children 12 years or younger: ask a doctor

Inactive Ingredients

Butylene Glycol, Caprylyl Glycol, Carbomer, Cetyl Alcohol, Chamomilla recutita (Matricaria) Flower Extract, Citrus aurantium Dulcis (Sweet Orange) Peel Oil, Cocos nucifera (Coconut) Oil, Creatine Monohydrate, Dimethicone, Eucalyptus globulus Leaf Oil, Fragrance, Glyceryl Stearate, Laureth-4, Phenoxyethanol, Purified Water, Salvia officinalis (Sage) Extract, Sodium Laureth Sulfate, Stearic Acid, Triethanolamine.